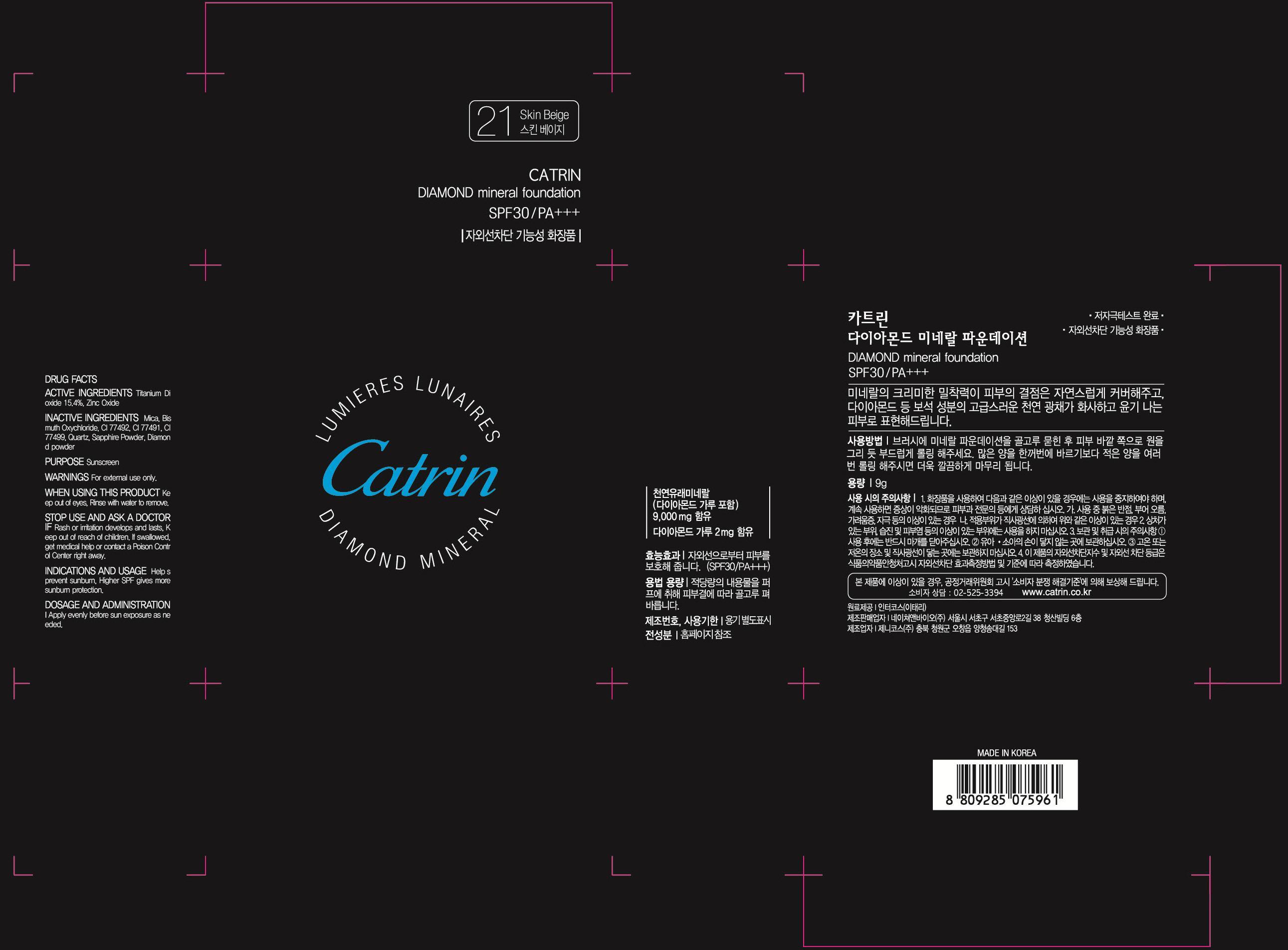 DRUG LABEL: CATRIN DIAMOND MINERAL FOUNDATION
NDC: 69058-010 | Form: POWDER
Manufacturer: Nature&Bio Co., Ltd.
Category: otc | Type: HUMAN OTC DRUG LABEL
Date: 20150113

ACTIVE INGREDIENTS: Titanium Dioxide 1.38 g/9 g; Zinc Oxide 1.17 g/9 g
INACTIVE INGREDIENTS: Mica

ACTIVE INGREDIENT

Active ingredients: Titanium Dioxide 15.4%, Zinc Oxide 13%

INACTIVE INGREDIENT

Inactive ingredients: Mica, Bismuth Oxychloride, CI 77492, CI 77491, CI 77499, Quartz, Sapphire Powder, Diamond powder

PURPOSE

Purpose: Sunscreen

WARNINGS

For external use only. When using this product: Keep out of eyes, Rinse with water to remove. Stop use and ask a doctor if: Rash or irritation develops and lasts, Keep out of reach of children. If swallowed, get medical help or contact a Poison Control Center right away.

KEEP OUT OF REACH OF CHILDREN

INDICATIONS & USAGE

Indications and usage: Helps prevent sunburn, Higher SPF gives moresunburn protection.

DOSAGE & ADMINISTRATION

Dosage and administration: Apply evenly before sun exposure as needed.

PACKAGE LABEL.PRINCIPAL DISPLAY PANEL

Image of carton